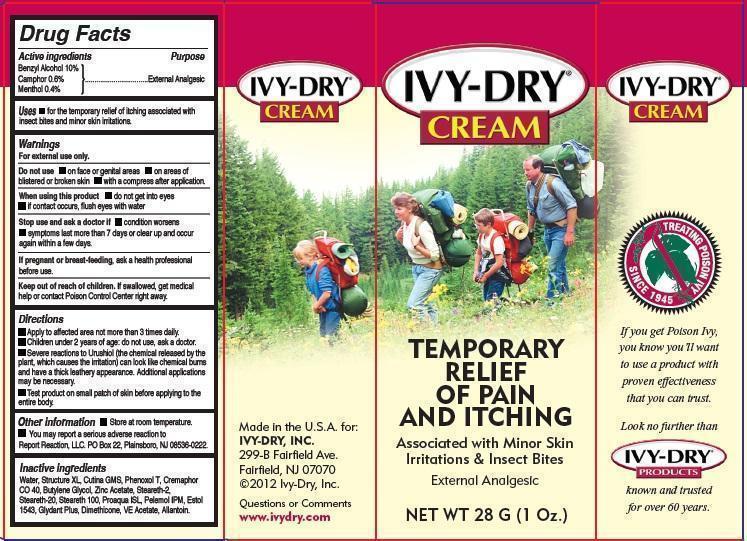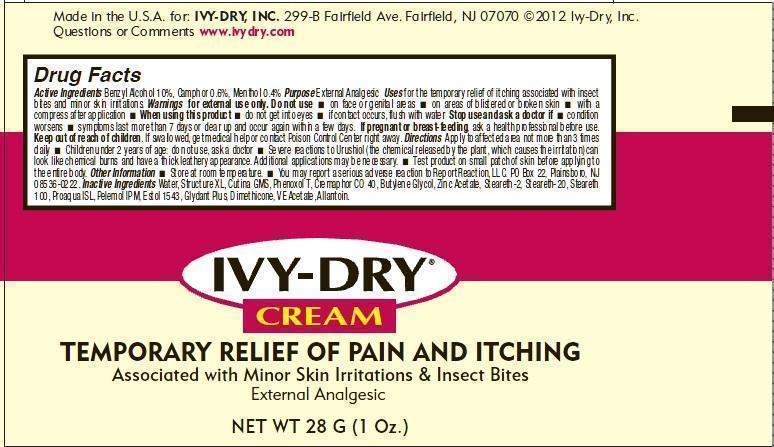 DRUG LABEL: Ivy Dry
NDC: 49546-201 | Form: CREAM
Manufacturer: Ivy Dry, Inc.
Category: otc | Type: HUMAN OTC DRUG LABEL
Date: 20191226

ACTIVE INGREDIENTS: BENZYL ALCOHOL 10 g/100 g; CAMPHOR (SYNTHETIC) 0.6 g/100 g; MENTHOL 0.4 g/100 g
INACTIVE INGREDIENTS: WATER; GLYCERYL MONOSTEARATE; BUTYLENE GLYCOL; ZINC ACETATE; STEARETH-2; STEARETH-20; STEARETH-100; DMDM HYDANTOIN; DIMETHICONE; ALLANTOIN

Ivy Dry Cream

Active Ingredients

Benzyl Alcohol 10%
Camphor 0.6%
Menthol 0.4%

Purpose

External Analgesic

Uses

for the temporary relief of itching associated with insect bites and minor skin irritations.

Warnings

For external use only.

Do not use

- face or genital areas
- on a reas of blistered or broken skin
- with a compress after application

When using this product

do not get into eyes if contact occurs, flush eyes with water

Stop use and ask a doctor if

- condition worsens
- symptoms last more than 7 days or clear up and occur again within a few days.

If pregnant or breastfeeding

ask a health professional before use.

Keep out of reach of children.

If swallowed, get medical help or contact Poison Control Center right away.

Directions

- Apply to affected area not more than 3 times daily.
- Children under 2 years of age: do not use, ask a doctor.
- Severe reactions to Urushiol (the chemical released by the plant, which causes the irritation) can look like chemical burns and have a thick leathery appearance. Additional applications may be necessary.
- Test product on small patch of skin before applying to the entire body.

Other information

- Store at room temperature.
- You may report a serious adverse reaction to Report Reaction, LLC. PO Box 22, Plainsboro, NJ 08536-0222.

Inactive Ingredients

Water, Structure XL, Cutina GMS, Phenoxol T, Cremaphor CO 40, Butylene Glycol, Zinc Acetate, Steareth-2,
Steareth-20, Steareth 100, Proaqua ISL, Pelemol IPM, Estol 1543, Glydant Plus, Dimethicone, VE Acetate, Allantoin.

DESCRIPTION

Made in the U.S.A. for:
IVY-DRY, INC.
299-B Fairfield Ave.
Fairfield, NJ 07070
©2012 Ivy-Dry, Inc.
Questions or Comments
www.ivydry.com

If you get Poison Ivy,
you know you’ll want
to use a product with
proven effectiveness
that you can trust.
Look no further than
Ivy Dry Products
known and trusted
for over 60 years.

Product Labeling

TEMPORARY
RELIEF
OF PAIN
AND ITCHING
Associated with Minor Skin
Irritations and Insect Bites
External Analgesic